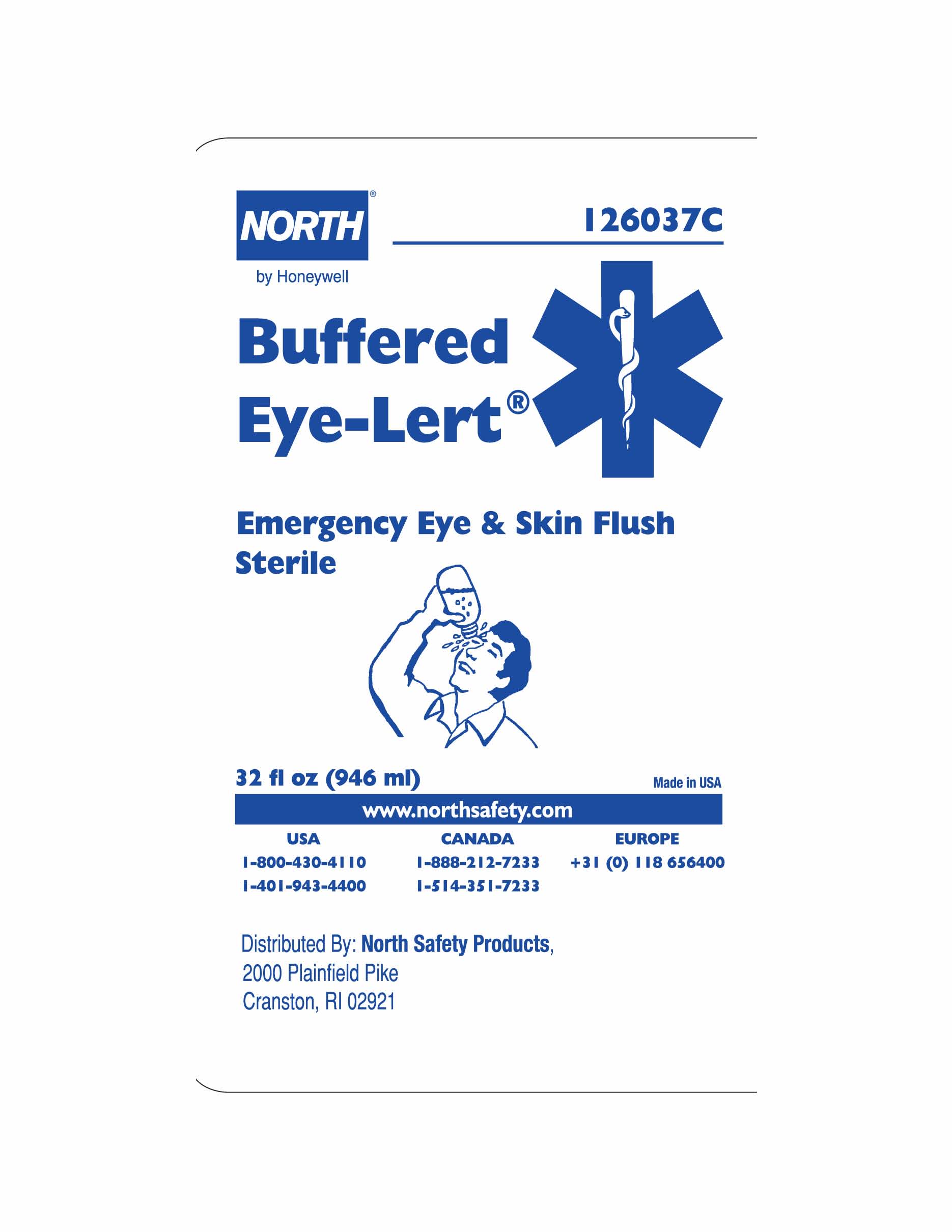 DRUG LABEL: Buffered Eye-Lert
NDC: 0498-0160 | Form: LIQUID
Manufacturer: North Safety Products 
Category: otc | Type: HUMAN OTC DRUG LABEL
Date: 20100713

ACTIVE INGREDIENTS: WATER 98 mL/100 mL
INACTIVE INGREDIENTS: SODIUM CHLORIDE; SODIUM PHOSPHATE, MONOBASIC, MONOHYDRATE; SODIUM PHOSPHATE, DIBASIC, HEPTAHYDRATE; EDETATE DISODIUM; BENZALKONIUM CHLORIDE

Buffered Eye-Lert

Active ingredient

Purified water 98%

Purpose

Emergency eyewash and skin flush

Uses

for flushing the eye and skin to reduce chances of severe injury caused by acid, alkali or particulate contamination.

Warnings

For external use only

Do not use

- for injection
- in intraocular surgery
- internally
- if solution changes color or becomes cloudy

When using this product

- avoid contamination, do not touch tip of container to any surface
- do not reuse
- once opened, discard
- obtain immediate medical treatment for all open wounds in or near the eyes

Ask doctor if you have

- eye pain
- changes in vision
- redness or irritation of the eye after use
- an injury caused by an alkai
- condition worsens or persists

KEEP OUT OF REACH OF CHILDREN

If swallowed, get medical help or contact a Poison Control center right away.

Directions

- do not dilute solution or reuse bottle
- hold container a few inches above the eye or skin
- control flow of solution by pressure on bottle
- flush affected area as needed a minimum of 20 minutes

Other information

- tamper evident: do not use if twist off top is broken or missing
- not for use as a contact lens solution
- twist cap to open
- use before expiration date marked on bottle
- store at room temperature, 15o to 30oC (59o to 86o)

Inactive ingredients

benzalkonium chloride, edetate disodium dihydrate, sodium chloride, sodium phosphate dibasic heptahydrate, sodium phosphate monobasic monohydrate

Questions

Questions or comments? Call toll free number 1-800-130-4110